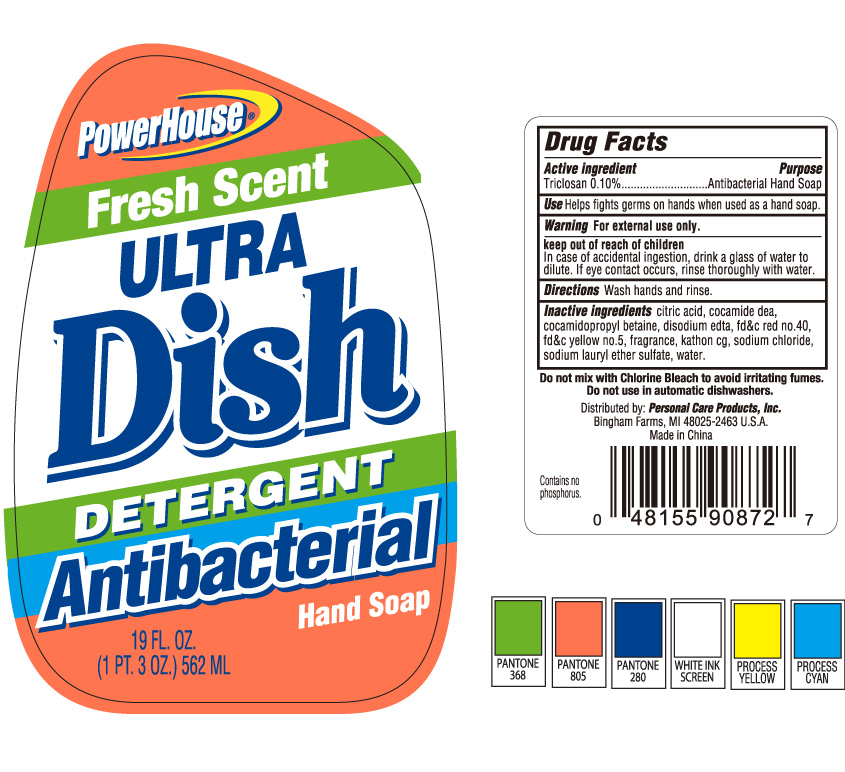 DRUG LABEL: Powerhouse Fresh Scent Ultra Dish
NDC: 29500-9087 | Form: SOAP
Manufacturer: Personal Care Products
Category: otc | Type: HUMAN OTC DRUG LABEL
Date: 20111229

ACTIVE INGREDIENTS: TRICLOSAN .562 mL/562 mL
INACTIVE INGREDIENTS: CITRIC ACID MONOHYDRATE; COCO DIETHANOLAMIDE; COCAMIDOPROPYL BETAINE; EDETATE DISODIUM; FD&C RED NO. 40; FD&C YELLOW NO. 5; SODIUM CHLORIDE; WATER

Powerhouse Fresh Scent Ultra Dish

Active Ingredient

Triclosan 0.10%

Purpose

Antibacterial Hand Soap

Keep out of reach of children

In case of accidental ingestion, drink a glass of water to dilute. If eye contact occurs, rinse thoroughly with water.

Use

Helps fights germs on hands when used as a hand soap.

Warning

For external use only

Directions

Wash hands and rinse.

Inactive Ingredients:

PACKAGE LABEL

Powerhouse Fresh Scent Ultra Dish Detergent Antibacterial Hand Soap

19 fl oz.

(1 pt.3 oz) 562 ml